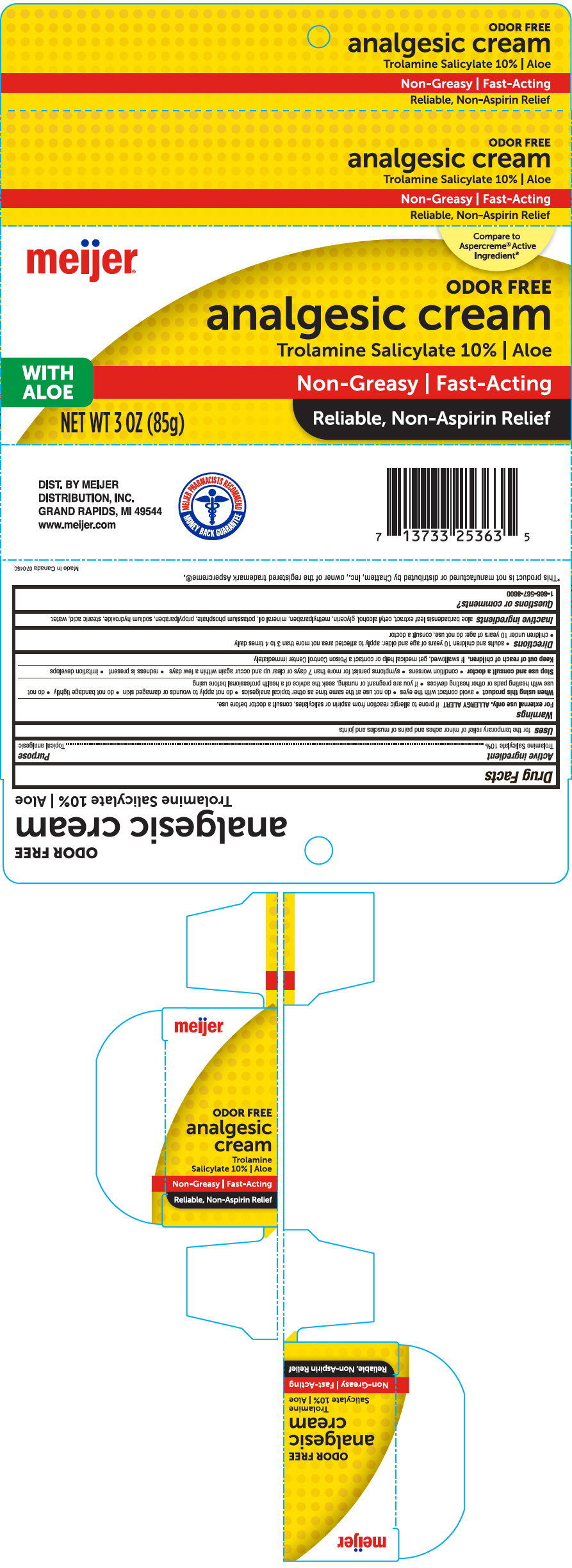 DRUG LABEL: Meijer Analgesic with Aloe
NDC: 41250-418 | Form: CREAM
Manufacturer: Meijer Distribution, Inc
Category: otc | Type: HUMAN OTC DRUG LABEL
Date: 20241107

ACTIVE INGREDIENTS: Trolamine Salicylate 100 mg/1 g
INACTIVE INGREDIENTS: ALOE VERA LEAF; Cetyl Alcohol; Glycerin; Methylparaben; Mineral Oil; POTASSIUM PHOSPHATE, UNSPECIFIED FORM; Propylparaben; Sodium Hydroxide; Stearic Acid; Water

Meijer® Analgesic Cream with Aloe
Topical Analgesic

Drug Facts

Active ingredients

Trolamine Salicylate 10%

Purpose

Topical Analgesic

Uses

for the temporary relief of minor aches and pains of muscles and joints

Warnings

For external use only.

ALLERGY ALERT if prone to allergic reaction from aspirin or salicylates, consult a doctor before use.

When using this product

- avoid contact with the eyes
- do not use at the same time as other topical analgesics
- do not apply to wounds or damaged skin
- do not bandage tightly
- do not use with heating pads or other heating devices
- if you are pregnant or nursing, seek the advice of a health professional before using

Stop use and consult a doctor

- condition worsens
- symptoms persist for more than 7 days or clear up and occur again within a few days
- redness is present
- irritation develops

PREGNANCY OR BREAST FEEDING

If you are pregnant or nursing a baby, seek the advice of a health professional before using this product.

Keep out of reach of children. If swallowed, get medical help or contact a Poison Control Center immediately

Directions

- Adults and children 10 years of age and older: apply to affected area not more than 4 times daily
- children under 10 years of age: do not use, consult a doctor

Inactive ingredients

Aloe Barbadensis Leaf Extract, Cetyl Alcohol, Glycerin, Methylparaben, Mineral Oil, Potassium Phosphate, Propylparaben, Sodium Hydroxide, Stearic Acid, Water.

Questions or comments?

1-866-567-8600

DIST. BY MEIJER
DISTRIBUTION, INC.
GRAND RAPIDS, MI 49544

PRINCIPAL DISPLAY PANEL - 85 g Tube Carton

meijer®

Compare to
Aspercreme® Active
Ingredient*

ODOR FREE
analgesic cream
Trolamine Salicylate 10% | Aloe

WITH
ALOE
Non-Greasy | Fast-Acting

NET WT 3 OZ (85g)
Reliable, Non-Aspirin Relief